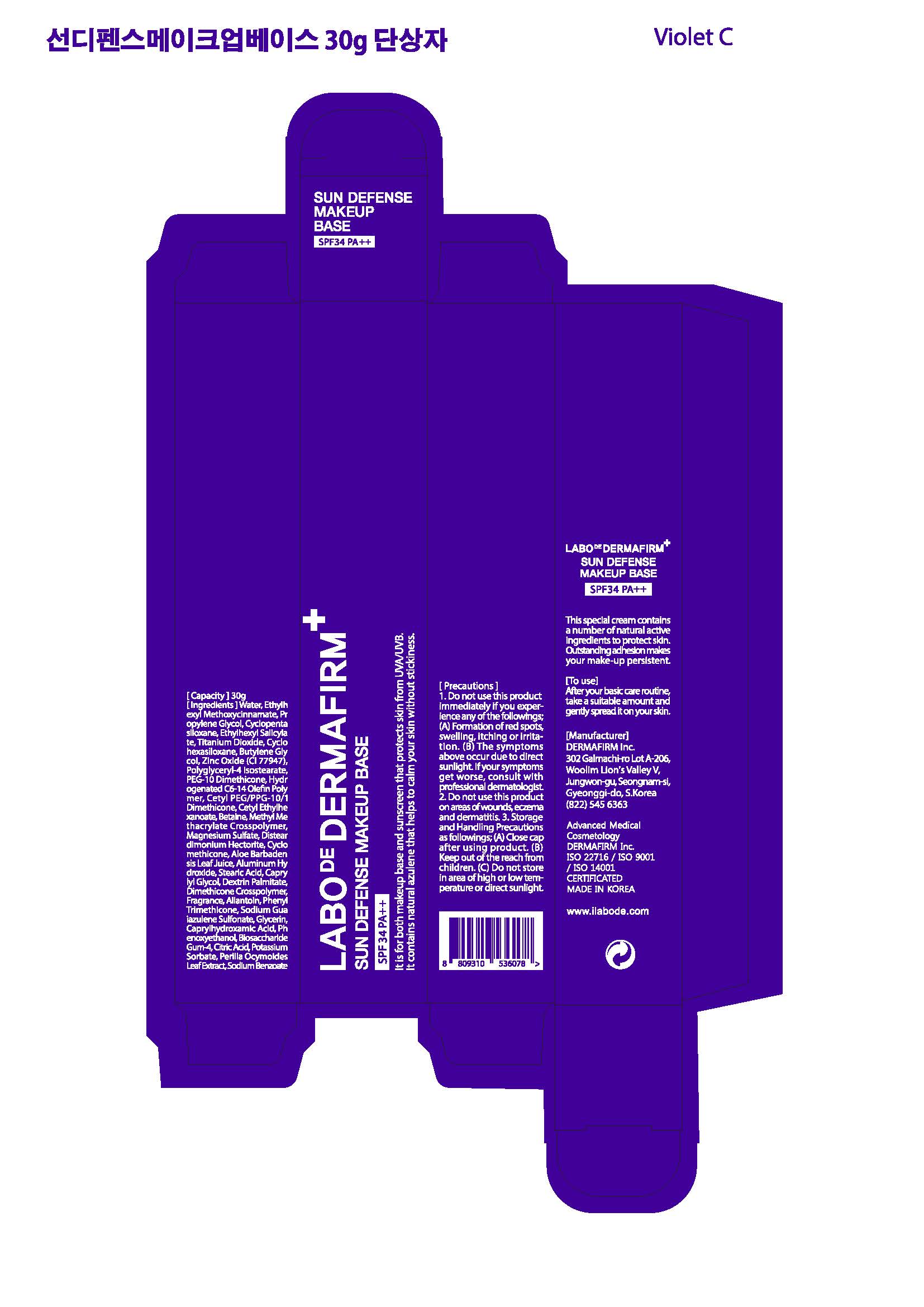 DRUG LABEL: LABODE DERMAFIRM SUN DEFENSE MAKE UP BASE
NDC: 71638-0014 | Form: CREAM
Manufacturer: Dermafirm INC.
Category: otc | Type: HUMAN OTC DRUG LABEL
Date: 20191203

ACTIVE INGREDIENTS: ZINC OXIDE 1.96 g/100 g; OCTISALATE 5 g/100 g; TITANIUM DIOXIDE 4.15 g/100 g; OCTINOXATE 7.5 g/100 g
INACTIVE INGREDIENTS: WATER; GLYCERIN

Dermafirm - LABODE DERMAFIRM SUN DEFENSE MAKE UP BASE (71638-0013)

ACTIVE INGREDIENT

Ethylhexyl Methoxycinnamate(Octinoxate), Ethylhexyl Salicylate(Octisalate), Titanium Dioxide, Zinc Oxide

INACTIVE INGREDIENT

Water, Propylene Glycol, Cyclohexasiloxane, Butylene Glycol, Polyglyceryl-4 Isostearate, PEG-10 Dimethicone, Hydrogenated Poly(C6-14 Olefin), Cetyl PEG/PPG-10/1 Dimethicone, Cetyl Ethylhexanoate, Betaine, Cyclomethicone, Magnesium Sulfate, Disteardimonium Hectorite, Methyl Methacrylate Crosspolymer, Aluminum Hydroxide, Stearic Acid, Caprylyl Glycol, Dextrin Palmitate, Dimethicone Crosspolymer, Phenyl Trimethicone, Sodium Guaiazulene Sulfonate, Glycerin, Caprylhydroxamic Acid, Allantoin, Aloe Barbadensis Leaf Juice, Perilla Ocymoides Leaf Extract, Phenoxyethanol, Biosaccharide Gum-4, Citric Acid, Potassium Sorbate, Sodium Benzoate, Fragrance

PURPOSE

Helps prevent sunburn.

Helps improve skin tone and keep moisturized.

keep out of reach of the children

INDICATIONS AND USAGE

After the basic skincare routine, apply a suitable amount and gently spread.

When using this product keep out of eyes. Rinse with water to remove.

Stop use and ask a doctor if rash or irritation develops and lasts.

DOSAGE AND ADMINISTRATION

for external use only